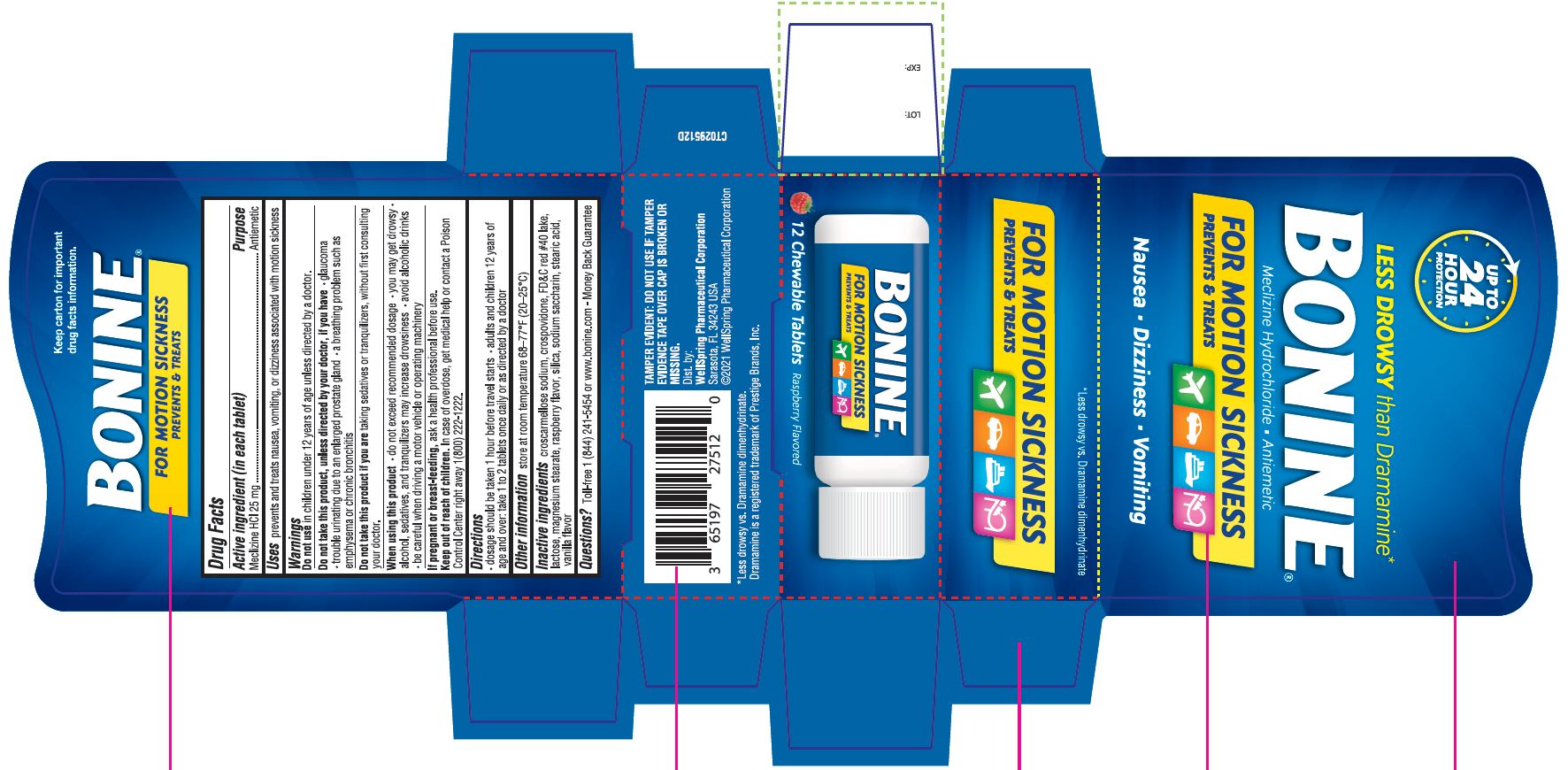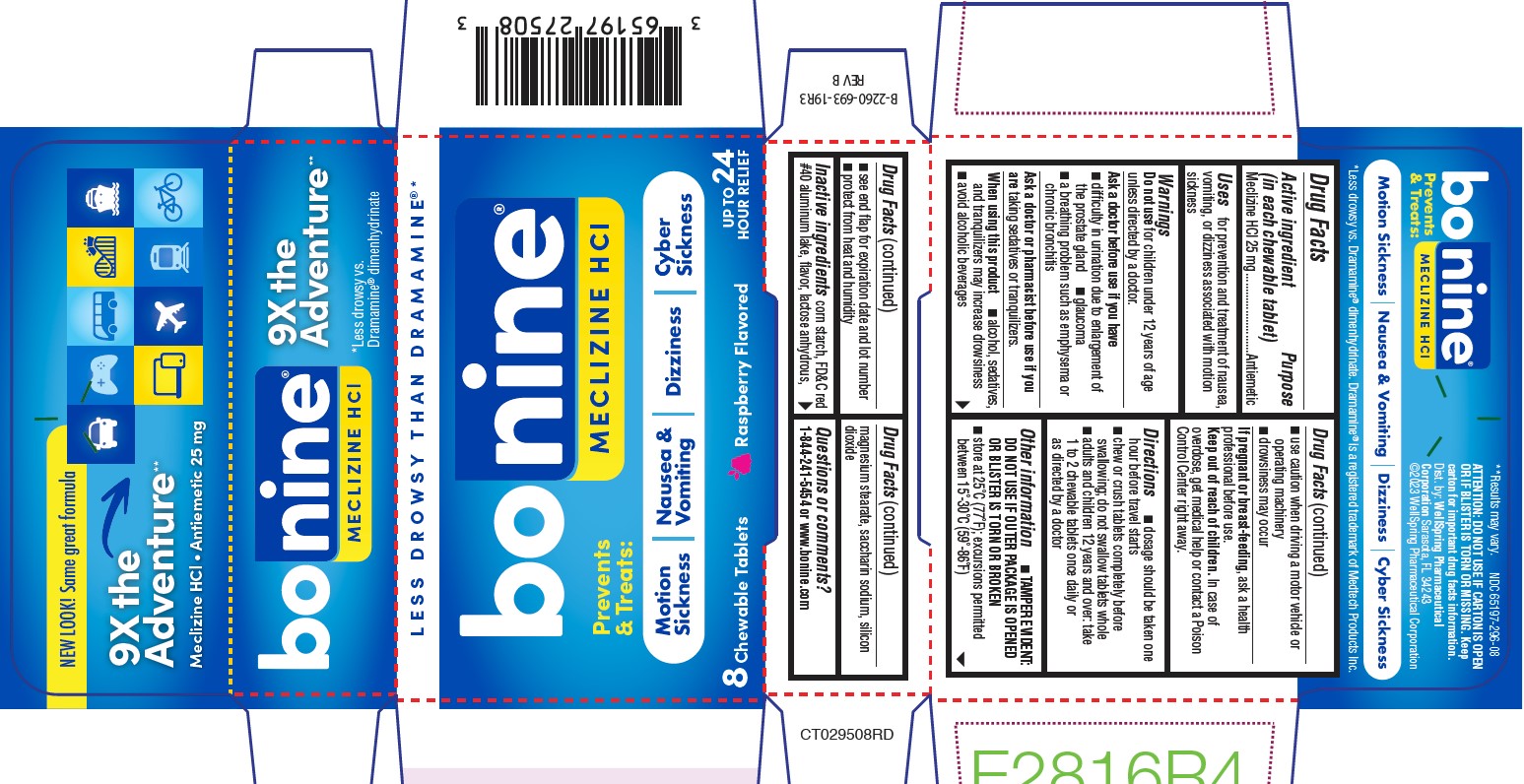 DRUG LABEL: BONINE
NDC: 65197-275 | Form: TABLET, CHEWABLE
Manufacturer: WellSpring Pharmaceutical Corporation
Category: otc | Type: HUMAN OTC DRUG LABEL
Date: 20250321

ACTIVE INGREDIENTS: MECLIZINE HYDROCHLORIDE 25 mg/1 1
INACTIVE INGREDIENTS: CROSCARMELLOSE SODIUM; CROSPOVIDONE; FD&C RED NO. 40; MAGNESIUM STEARATE; SILICON DIOXIDE; SACCHARIN SODIUM; STEARIC ACID; LACTOSE MONOHYDRATE; RASPBERRY; VANILLA

BONINE®
MECLIZINE HYDROCHLORIDE • ANTIEMETIC
Nausea - Dizziness - Vomiting
*Less drowsy than Dramamine

Active ingredient (in each tablet)

Meclizine HCl 25 mg

Purpose

Antiemetic

Uses

prevents and treats nausea, vomiting or dizziness associated with motion sickness

Warnings

Do not use

in children under 12 years of age unless directed by a doctor.

Do not take this product, unless directed by a doctor, if you have

- glaucoma
- trouble urinating due to an enlarged prostate gland
- a breathing problem such as emphysema or chronic bronchitis

Do not take this product if you are

taking sedatives or tranquilizers, without first consulting your doctor.

When using this product

- do not exceed recommended dosage
- you may get drowsy
- alcohol, sedatives, and tranquilizers may increase drowsiness
- avoid alcoholic drinks
- be careful when driving a motor vehicle or operating machinery

If pregnant or breast-feeding,

ask a health professional before use.

Keep out of reach of children.

In case of overdose, get medical help or contact a Poison Control Center right away.

Directions (65197-275)

- dosage should be taken one hour before travel starts
- adults and children 12 years of age and over: take 1 to 2 tablets once daily or as directed by a doctor

Directions (65197-296)

- dosage should be taken one hour before travel starts
- chew or crush tablets completely before swallowing; do not swallow tablets whole
- adults and children 12 years and over: take 1 to 2 chewable tablets once daily or as directed by a doctor

Other information

TAMPER EVIDENT: DO NOT USE IF OUTER PACKAGE IS OPENED OR BLISTER IS TORN OR BROKEN

store at 25°C (77°F); excursions permitted between 15°-30°C (59°-86°F)

Inactive ingredients (65197-275)

croscarmellose sodium, crospovidone, FD&C red #40 lake, lactose, magnesium stearate, raspberry flavor, silica, sodium saccharin, stearic acid, vanilla flavor.

Inactive Ingredients (65197-296)

corn starch, FD&C red #40 aluminum lake, flavor, lactose anhydrous, magnesium stearate, saccharin sodium, silicon dioxide

Questions?

1 (844) 241-5454 or www.bonine.com

TAMPER EVIDENT 65197-275

TAMPER EVIDENT: DO NOT USE IF TAMPER EVIDENCE TAPE OVER CAP IS BROKEN OR MISSING.

TAMPER EVIDENT 65197-296

ATTENTION: DO NOT USE IF CARTON IS OPEN OR IF BLISTER IS TORN OR MISSING.

Keep Carton for important drug facts information.

Dist. by:

WellSpring Pharmaceutical
Corporation Sarasota, FL 34243
©2023 WellSpring Pharmaceutical Corporation

PACKAGE LABEL.PRINCIPAL DISPLAY PANEL 65197-275

UP TO 24 HOUR PROTECTION

BONINE®
MECLIZINE HYDROCHLORIDE • ANTIEMETIC
Nausea - Dizziness - Vomiting
*Less drowsy than Dramamine

Bonine 12 ct

PACKAGE LABEL.PRINCIPAL DISPLAY PANEL 65197-296

NEW LOOK! Same great formula

9X the Adventure**

**Results may vary.

Meclizine HCL • Antiemetic 25mg

*Less drowsy than Dramamine ®

BONINE®

MECLIZINE HCL

Prevents & Treats: Motion Sickness / Nausea & Vomiting / Dizziness / Cyber Sickness

Up to 24 Hours Relief

Bonine 8ct Blue new Design